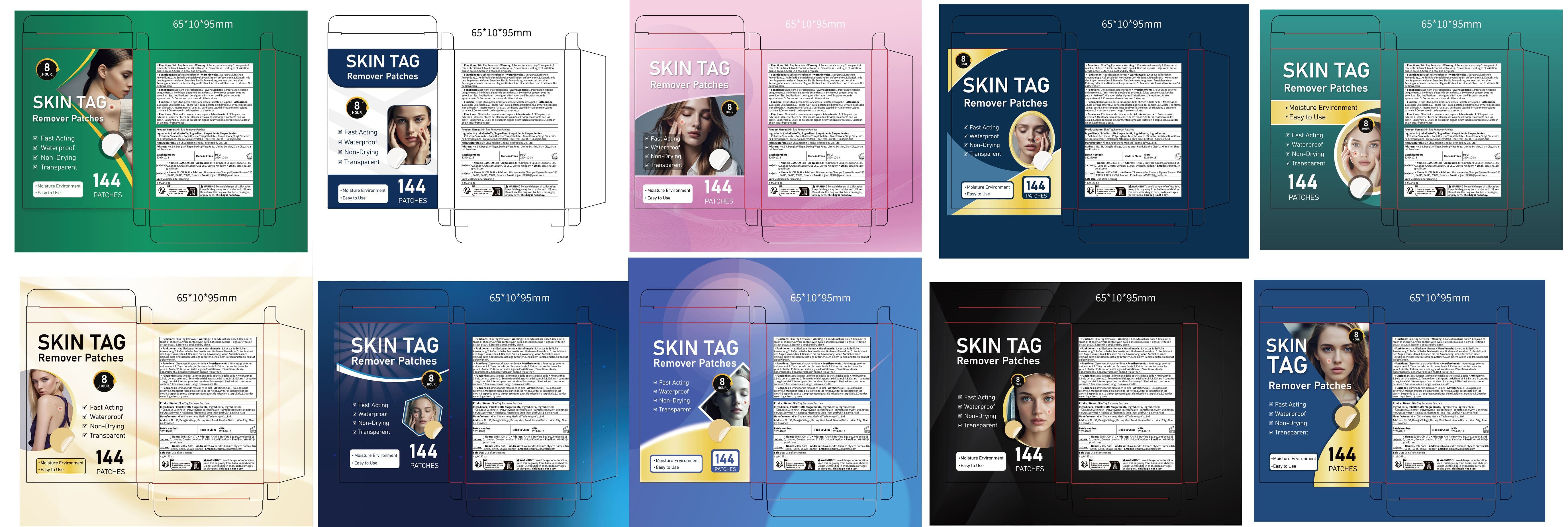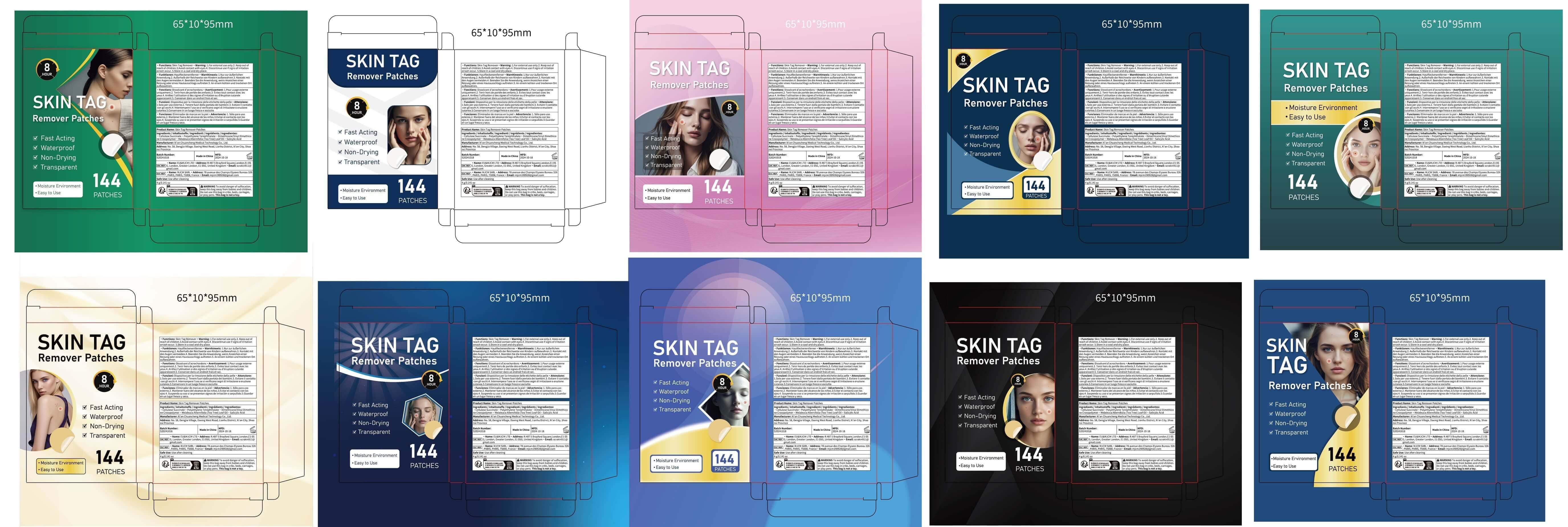 DRUG LABEL: Skin Tag Remover Patches
NDC: 84758-003 | Form: PATCH
Manufacturer: Xi'an Chuancheng Medical Technology Co., Ltd.
Category: otc | Type: HUMAN OTC DRUG LABEL
Date: 20241031

ACTIVE INGREDIENTS: SALICYLIC ACID 0.2 g/4 g
INACTIVE INGREDIENTS: POLYETHYLENE TEREPHTHALATE (INTRINSIC VISCOSITY 0.40-0.70) 2.66 g/4 g; CELLULOSE SULFATE 0.53 g/4 g; DIMETHICONE/VINYL DIMETHICONE CROSSPOLYMER (SOFT PARTICLE) 0.33 g/4 g; MELALEUCA ALTERNIFOLIA (TEA TREE) LEAF OIL 0.26 g/4 g

Active Ingredient

Salicylic Acid 5%

PURPOSE

Wart/Skin Tag remover

How To Use

1. Prep your skin. Cleanse and dry pimple area.
2.Patch the tag. Leave on for 6-8 hours.
3.Watch it work. Peel off when patch turns white.

Warnings

Warnings: to avoid danger of suffocation.keep this plastic bag away from babies andchildren.do not use this bag incribs, beds carriages or play pens. this bag is not a toy.

Stop Use

Stop using and ask a doctor if a rash and/or irritationoccurs.

DO NOT USE

on damaged or broken skin

WHEN USING

keep out of eyes. Rinse with water to remove.

Keep Oot Of Reach Of Children

If swallowed, get medical help or contact a Poison Control Center right away.

INACTIVE INGREDIENT

Cellulose Succinate
Polyethylene Terephthalate
Dimethicone/Vinyl Dimethicone Crosspolymer
Melaleuca Alternifolia (Tea Tree) Leaf Oil

DOSAGE & ADMINISTRATION

DOSAGE;Patch
Route of Administration:TOPCIAL